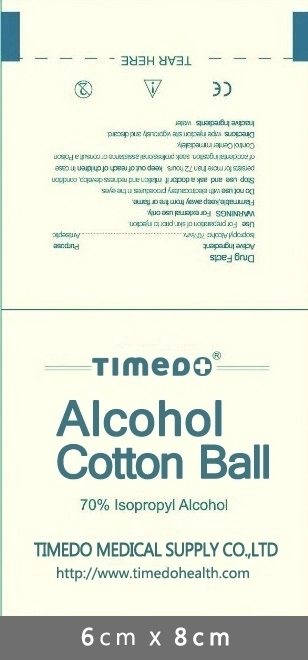 DRUG LABEL: Alcohol Cotton Ball
NDC: 76284-002 | Form: SWAB
Manufacturer: Ningbo Timedo Medical Supply Co.,Ltd.
Category: otc | Type: HUMAN OTC DRUG LABEL
Date: 20110629

ACTIVE INGREDIENTS: ISOPROPYL ALCOHOL 0.7 mL/1 1
INACTIVE INGREDIENTS: WATER 0.3 mL/1 1

TIMEDO ALCOHOL COTTON BALL 70% Isopropyl Alcohol TIMEDO MEDICAL SUPPLY CO., LTD. http://www.timedohealth.com

Active Ingredient

Isopropyl Alcohol 70%

Purpose

Antiseptic

Use

Use for preparation of the skin prior to an injection

Warnning

For External use only.

Flammable,keep away from fire or flame.

Do not use with electrocautery procedures in eyes.

Stop use and ask a doctor if irritation and redness develop,condition persists for more than 72 hours .

Keep out of reach of children in case of accidental ingestion,seek professional assistance or consult a Poison Control Center immediately.

Directions

wipe injection site vigorously and discard

Inactive Ingredients

Inactive Ingredients: Water

Keep out of reach of children in case of accidental ingestion,seek professional assistance or consult a Poison Control Center immediately.